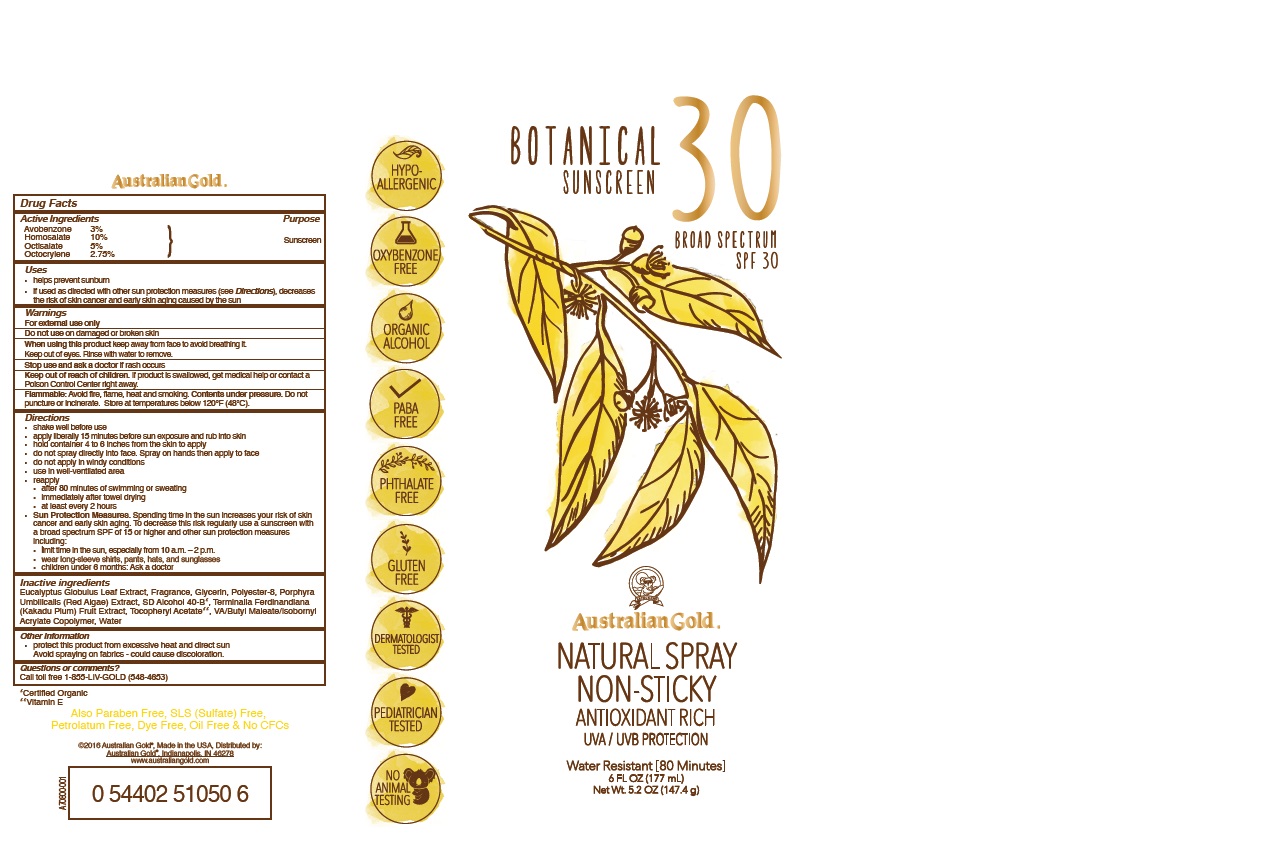 DRUG LABEL: Australian Gold
NDC: 13630-0199 | Form: SPRAY
Manufacturer: Prime Packaging Inc.
Category: otc | Type: HUMAN OTC DRUG LABEL
Date: 20211129

ACTIVE INGREDIENTS: AVOBENZONE 25.44 mg/1 mL; HOMOSALATE 84.8 mg/1 mL; OCTISALATE 42.4 mg/1 mL; OCTOCRYLENE 23.32 mg/1 mL
INACTIVE INGREDIENTS: BUTYL ACRYLATE/C16-C20 ALKYL METHACRYLATE/METHACRYLIC ACID/METHYL METHACRYLATE COPOLYMER; ALCOHOL; POLYESTER-8 (1400 MW, CYANODIPHENYLPROPENOYL CAPPED); PORPHYRA UMBILICALIS; KAKADU PLUM; .ALPHA.-TOCOPHEROL ACETATE; WATER; EUCALYPTUS GLOBULUS LEAF; GLYCERIN

Botanical Sunscreen Broad Spectrum SPF 30 Natural

Active Ingredients

Avobenzone 3%

Homosalate 10%

Octisalate 5%

Octocrylene 2.75%

Purpose

Sunscreen

Uses

- helps prevent sunburn
- if used as directed with other sun protection measures (see Directions), decreases the risk of skin cancer and early skin aging caused by the sun.

Warnings

For external use only

Do not use on damaged or broken skin

When using this product keep away from face to avoid breathing it

- Keep out of eyes. Rinse with water to remove

Stop use and ask a doctor if rash occurs

Keep out of reach of children. If product is swallowed, get medical help or contact a Poison Control Center right away.

OTHER SAFETY INFORMATION

Flammable: Avoid fire, flame, heat and smoking. Contents under presssure. Do not puncture or incinerate. Store at temperatures below 120ºC (48ºC).

Directions

- shake well before use
- Apply liberally 15 minutes before sun exposure and rub into skin
- hold container 4 to 6 inches from the skin to apply
- do not spray directly into face. Spray on hands then apply to face
- do not apply in windy conditions
- use in well-ventilated area
- reapply:
- after 80 minutes of swimming or sweating
- immediately after towel drying
- at least every 2 hours
- Sun Protection Measures. Spending time in the sun increases your risk of skin cancer and early skin aging. To decrease this risk, regularly use a sunscreen with a broad spectrum SPF of 15 or higher and other sun protection measures including:
- limit time in the sun, especially from 10 a. m. - 2 p. m.
- wear long-sleeve shirts, pants, hats, and sunglasses
- children under 6 months: Ask a doctor

Inactive Ingredients

Eucalyptus Globulus Leaf Extract, Fragrance, Glycerin, Polyester-8, Porphyra Umbilicalis Extract, SD Alcohol 40-B, Terminalia Ferdinandiana (Kakadu Plum) Fruit Extract, Tocopheryl Acetate, VA/Butyl Maleate/Isobornyl Acrylate Copolymer, Water

Other Information

- protect this product from excessive heat and direct sun
- Avoid spraying on fabrics - could cause discoloration

Question or comments?

Call toll free 1-855-LIV-GOLD (548-4653)